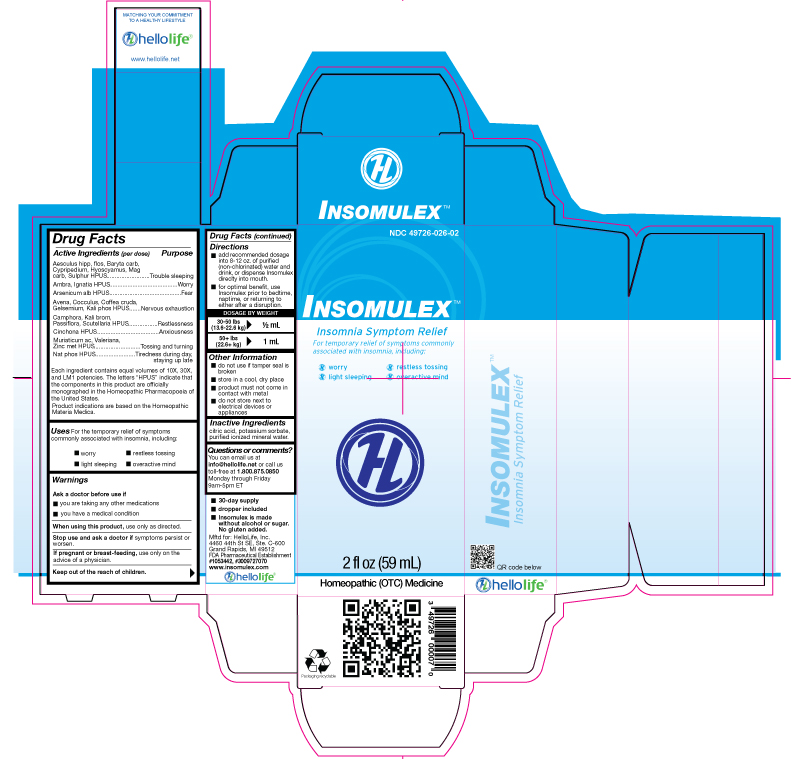 DRUG LABEL: Insomulex
NDC: 49726-026 | Form: LIQUID
Manufacturer: Hello Life, Inc.
Category: homeopathic | Type: HUMAN OTC DRUG LABEL
Date: 20181226

ACTIVE INGREDIENTS: AESCULUS HIPPOCASTANUM FLOWER 10 [hp_X]/59 mL; AMBERGRIS 10 [hp_X]/59 mL; AVENA SATIVA FLOWERING TOP 10 [hp_X]/59 mL; BARIUM CARBONATE 10 [hp_X]/59 mL; CAMPHOR (NATURAL) 10 [hp_X]/59 mL; CINCHONA OFFICINALIS BARK 10 [hp_X]/59 mL; ANAMIRTA COCCULUS SEED 10 [hp_X]/59 mL; ARABICA COFFEE BEAN 10 [hp_X]/59 mL; CYPRIPEDIUM PARVIFLORUM VAR. PUBESCENS ROOT 10 [hp_X]/59 mL; GELSEMIUM SEMPERVIRENS ROOT 10 [hp_X]/59 mL; HYOSCYAMUS NIGER 10 [hp_X]/59 mL; STRYCHNOS IGNATII SEED 10 [hp_X]/59 mL; POTASSIUM BROMIDE 10 [hp_X]/59 mL; POTASSIUM PHOSPHATE, DIBASIC 10 [hp_X]/59 mL; MAGNESIUM CARBONATE 10 [hp_X]/59 mL; HYDROCHLORIC ACID 10 [hp_X]/59 mL; SODIUM PHOSPHATE, DIBASIC, HEPTAHYDRATE 10 [hp_X]/59 mL; PASSIFLORA INCARNATA FLOWERING TOP 10 [hp_X]/59 mL; ARSENIC TRIOXIDE 10 [hp_X]/59 mL; SCUTELLARIA LATERIFLORA 10 [hp_X]/59 mL; SULFUR 10 [hp_X]/59 mL; VALERIAN 10 [hp_X]/59 mL; ZINC 10 [hp_X]/59 mL
INACTIVE INGREDIENTS: CITRIC ACID MONOHYDRATE; POTASSIUM SORBATE; WATER

Active Ingredients (per dose)

Aesculus hipp, flos, Baryta carb, Cypripedium, Hyoscyamus, Mag carb, Sulphur HPUS

Ambra, Ignatia HPUS

Arsenicum alb HPUS

Avena, Cocculus, Coffea cruda, Gelsemium, Kali phos HPUS

Camphora, Kali brom, Passiflora, Scutellaria HPUS

Cinchona HPUS

Muriaticum ac, Valeriana, Zinc met HPUS

Nat phos HPUS

Each ingredient contains equal volumes of 10X, 30X, and LM1 potencies. The letters "HPUS" indicate that the components in thsi prodct are officially monographed in the Homeopathic Pharmacopeia of the United States.

Product indications are based on Homeopathic Materia Medica.

Purpose

Aesculus hipp, flos, Baryta carb, Cypripedium, Hyoscyamus, Mag carb, Sulphur HPUS.....................................Trouble sleeping
Ambra, Ignatia HPUS...................................................................................................................................................Worry

Arsenicum alb HPUS....................................................................................................................................................Fear

Avena, Cocculus, Coffea cruda, Gelsemium, Kali phos HPUS....................................................................Nervous Exhaustion
Camphora, Kali brom, Passiflora, Scutellaria HPUS.............................................................................................Restlessness
Cinchona HPUS................................................................................................................................................Anxiousness
Muriaticum ac, Valeriana, Zinc met HPUS.................................................................................................Tossing and Turning
Nat phos HPUS..............................................................................................................Tiredness during day, staying up late

Each ingredient contains equal volumes of 10X, 30X, and LM1 potencies. The letters “HPUS” indicate that the components in this product are officially monographed in the Homeopathic Pharmacopoeia of the United States. Indications are based on Homeopathic Materia Medica.

Uses

For the temporary relief of symptoms commonly associated with insomnia, including:

- worry
- restless tossing
- light sleeping
- overactive mind

Warnings

Ask a doctor before use if

- you are taking any other medications
- you have a medical condition

When using this product, use only as directed.

Stop use and ask a doctor if symptoms persist or worsen.

PREGNANCY OR BREAST FEEDING

If pregnant or breast-feeding, use only on the advice of a physician.

Keep out of the reach of children.

Directions

- add recommended dosage into 8-12 oz. of purified (non-chlorinated) water and drink, or dispense Insomulex directly into mouth.
- for optimal benefit, use Insomulex prior to bedtime, naptime, or returning to either after a disruption.

Dosage by Weight:
30-50 lbs (13.6-22.6 kg) 1/2 mL
50+ lbs (22.6+ kg) 1 mL

Other Information

- do not use if tamper seal is broken
- store in a cool, dry place
- product must not come in contact with metal
- do not store next to electrical devices or appliances

Inactive Ingredients

citric acid, potassium sorbate, purified ionized mineral water

Questions or comments?

You can email us at info@hellolife.net or give us a call toll-free at 1.800.875.0850. Monday through Friday 9am-5pm.

DESCRIPTION

- 30-day supply
- dropper included
- Insomulex is made without alcohol or sugar. No gluten added.

Mftd for: HelloLife, LLC.
4460 44th St. SE, Ste. C-600
Grand Rapids, MI 49512
FDA Pharmaceutical Establishment
#1053442, #3009727070
www.insomulex.com

Principal Display Panel

NDC 49726-026-02

INSOMULEXTM

Insomnia Symptom Relief

For temporary relief of symptoms commonly associated with insomnia, including:

- worry
- restless tossing
- light sleeping
- overactive mind

2 FL OZ (59 mL)
Homeopathic (OTC) Medicine